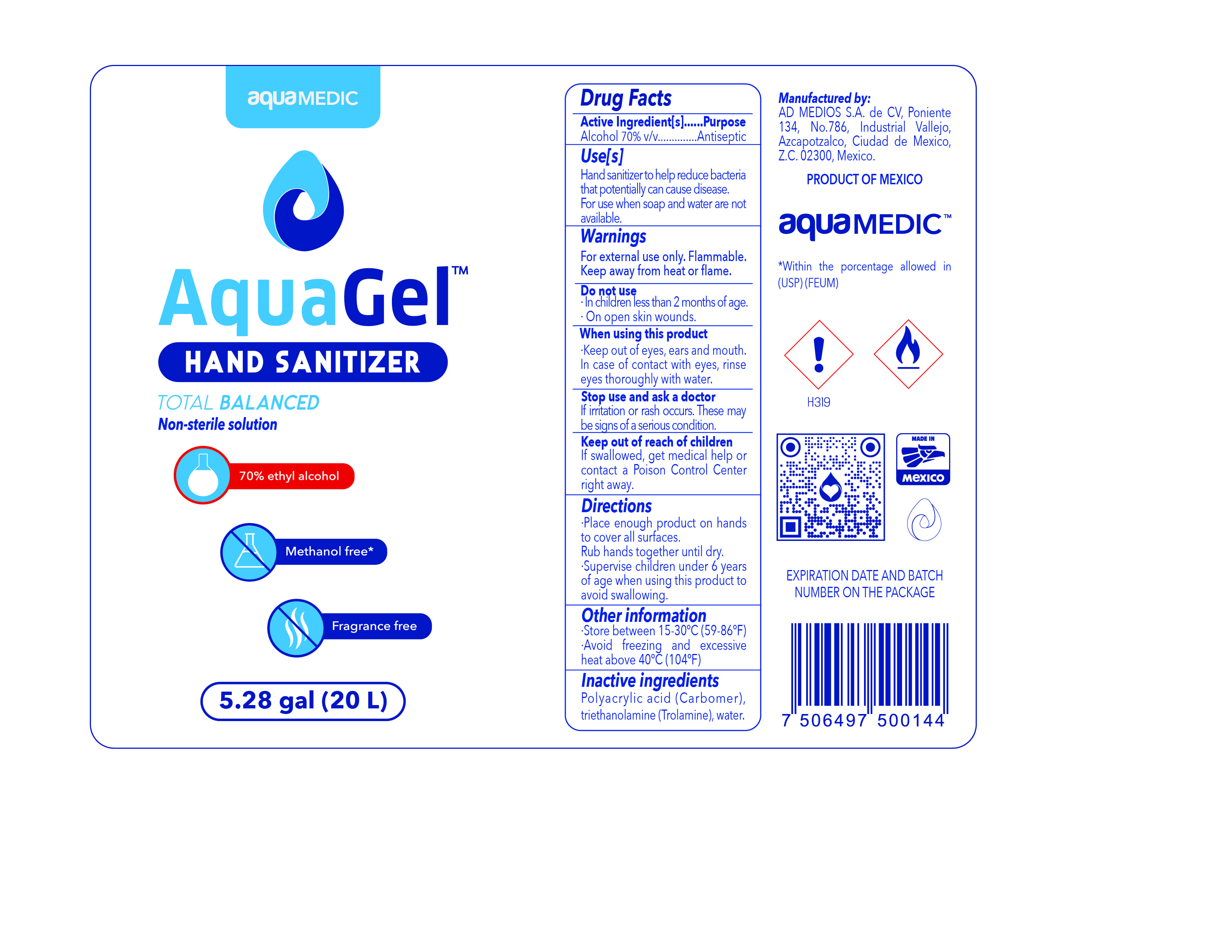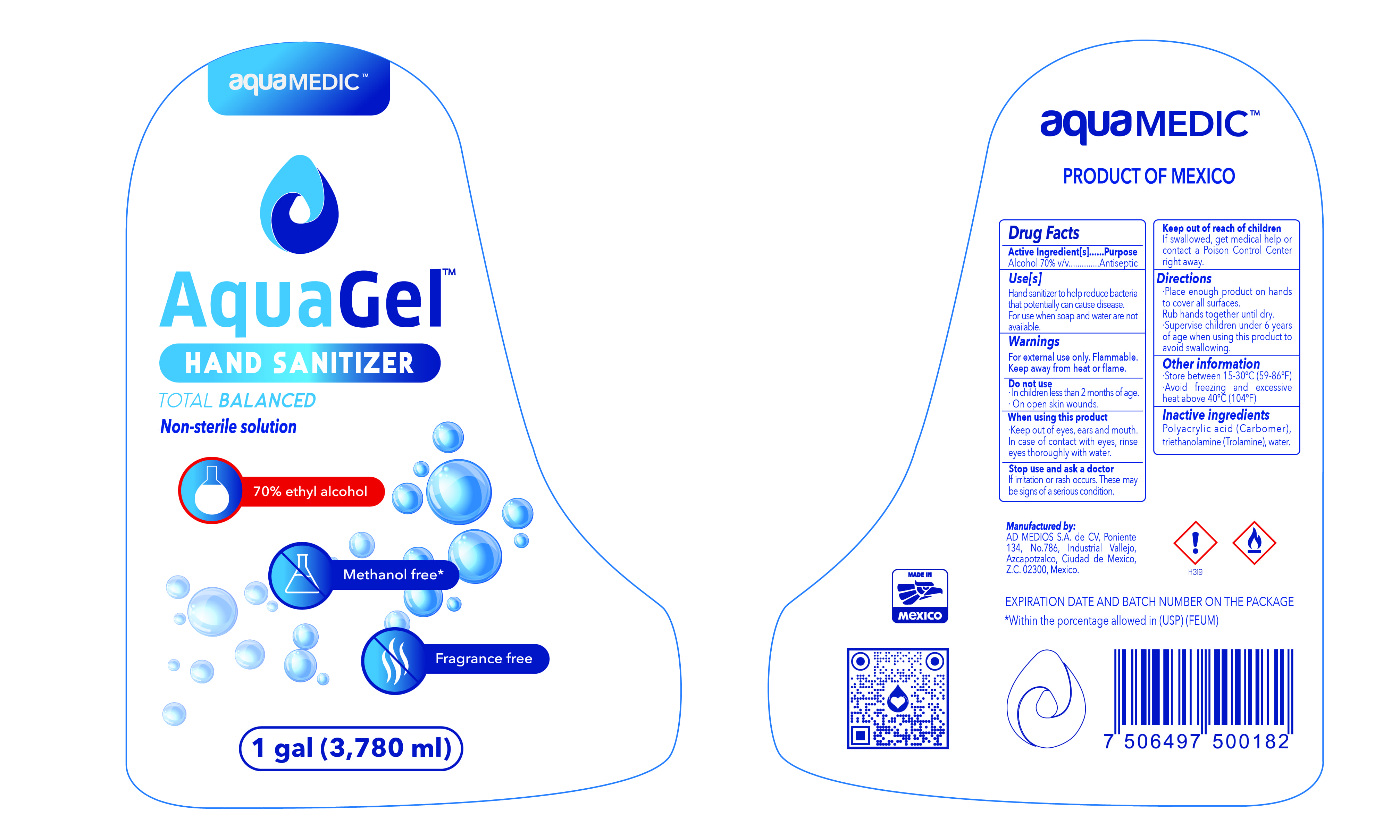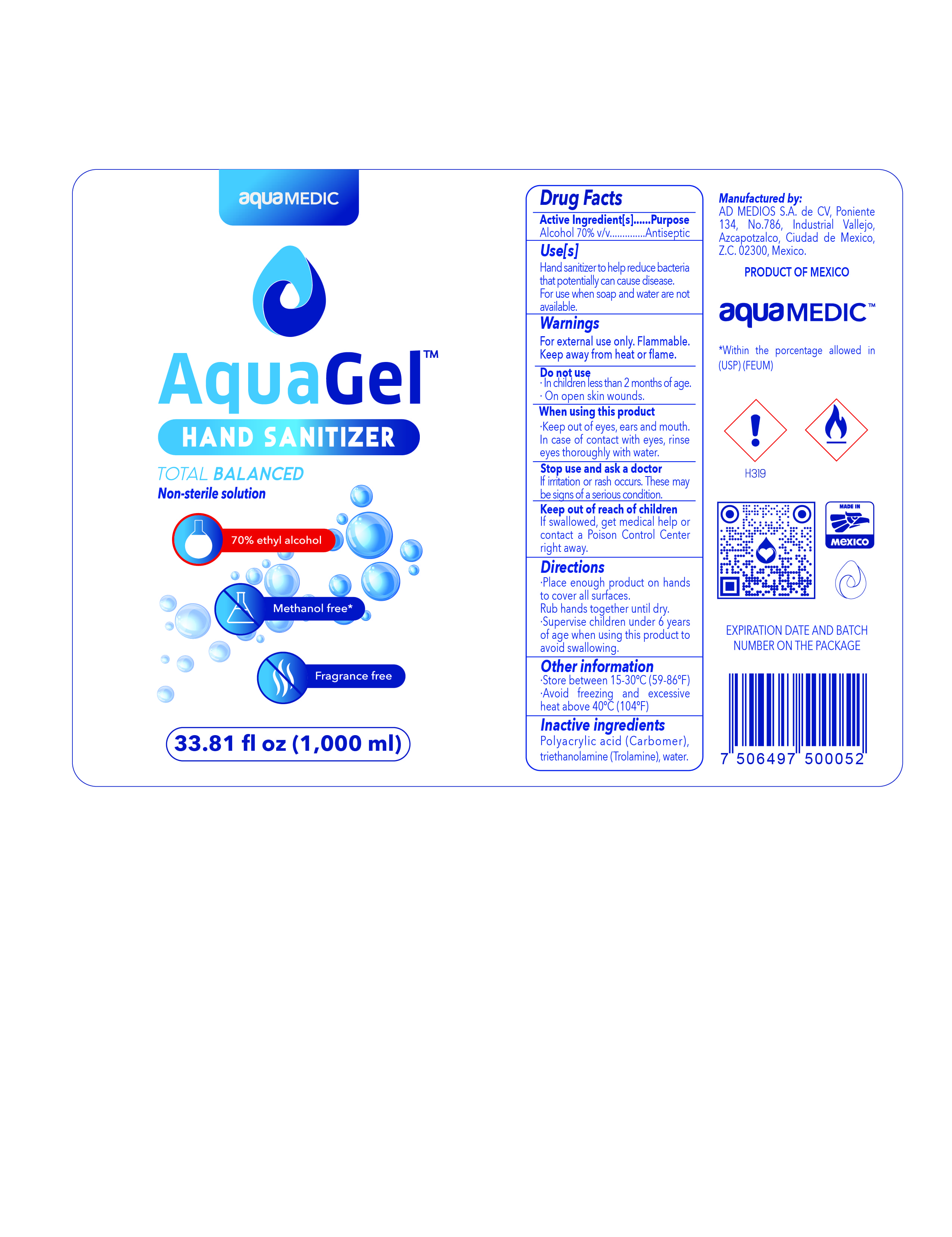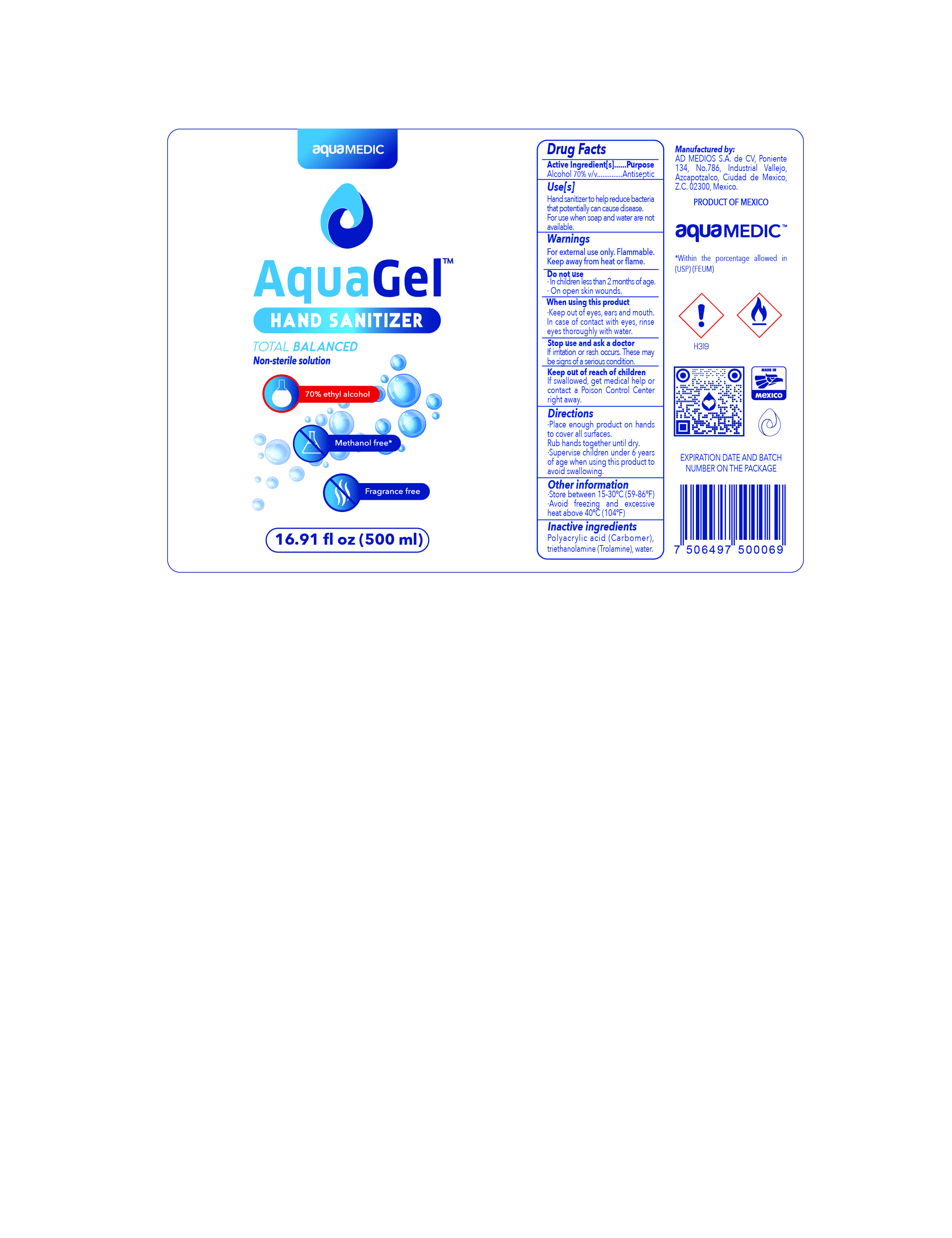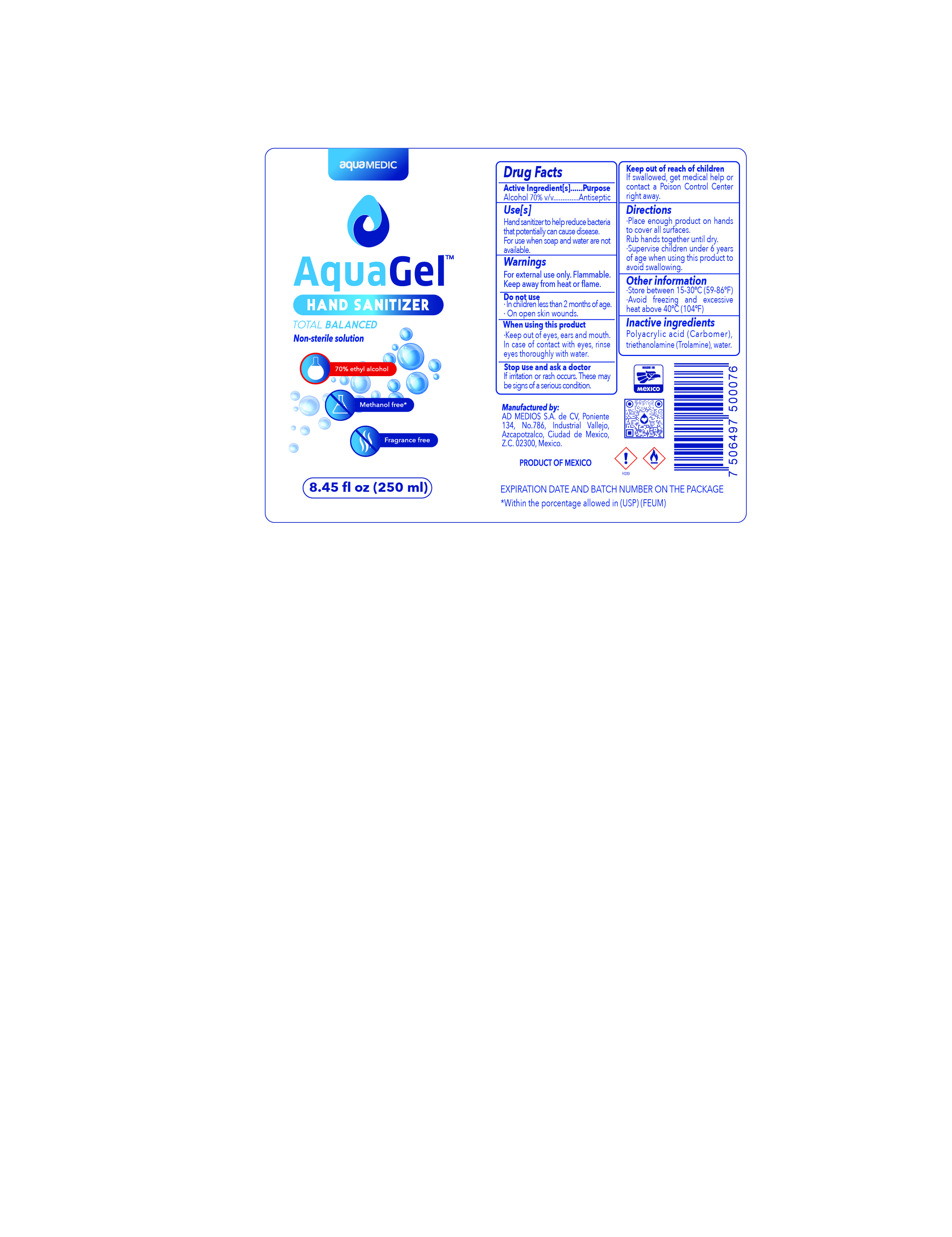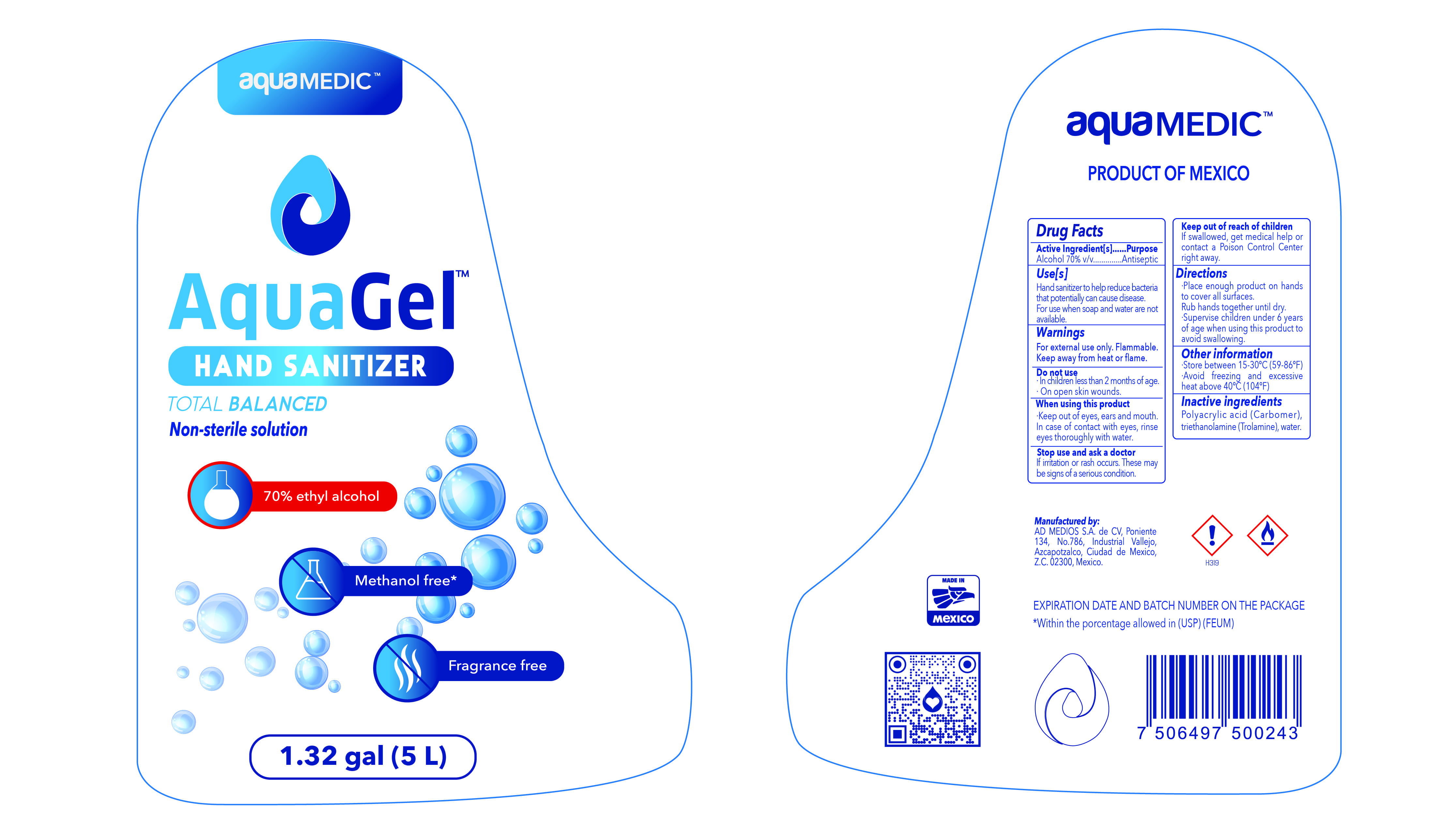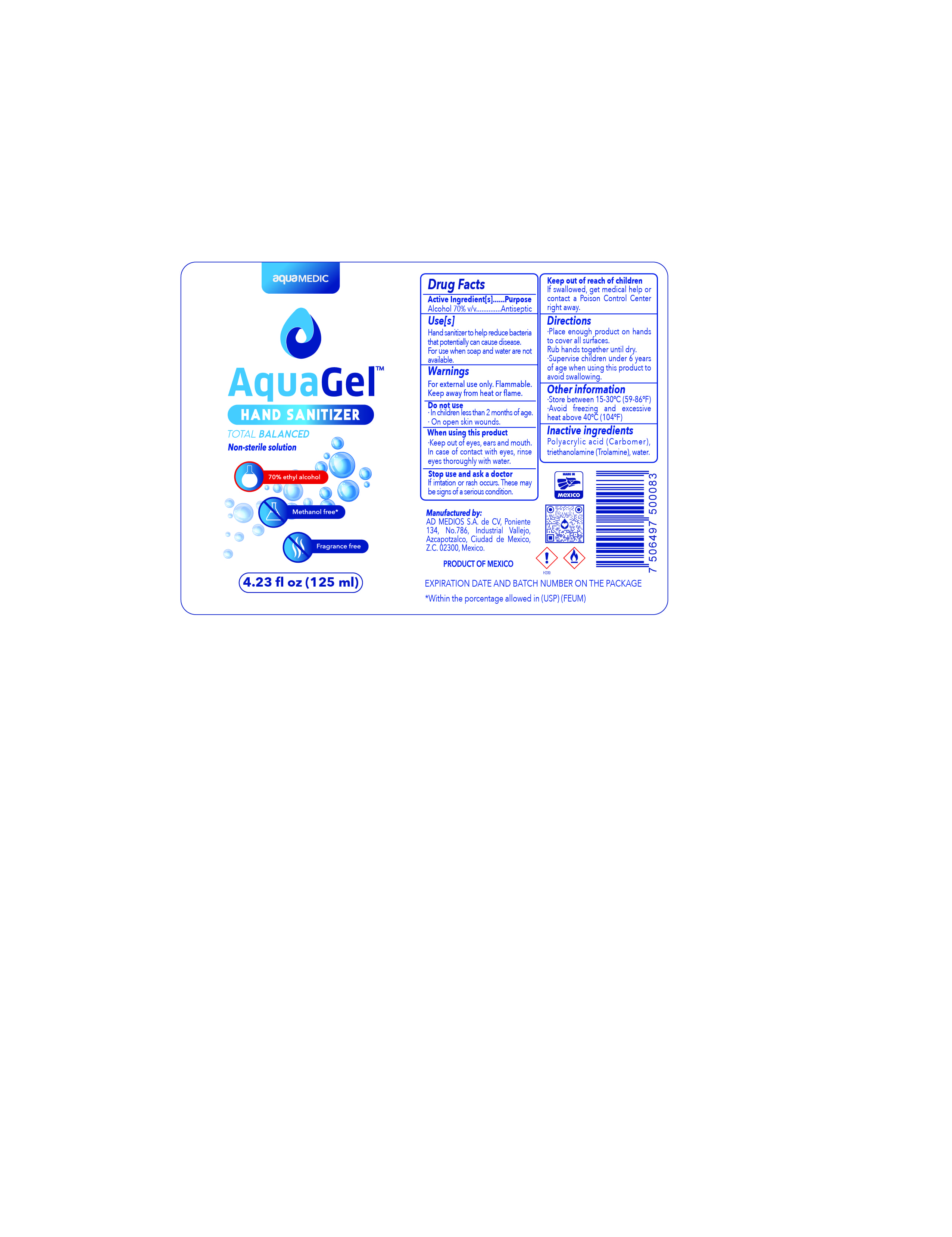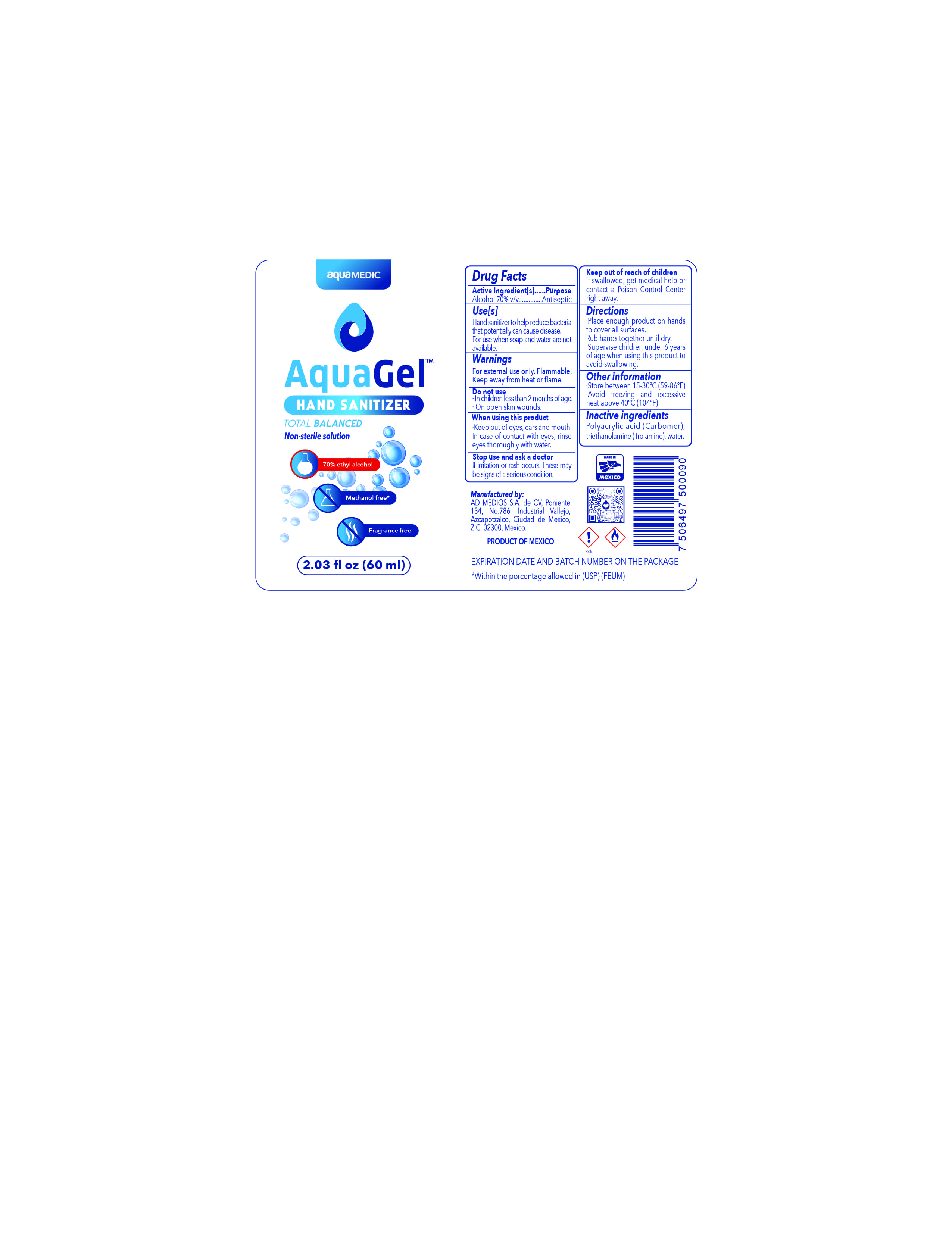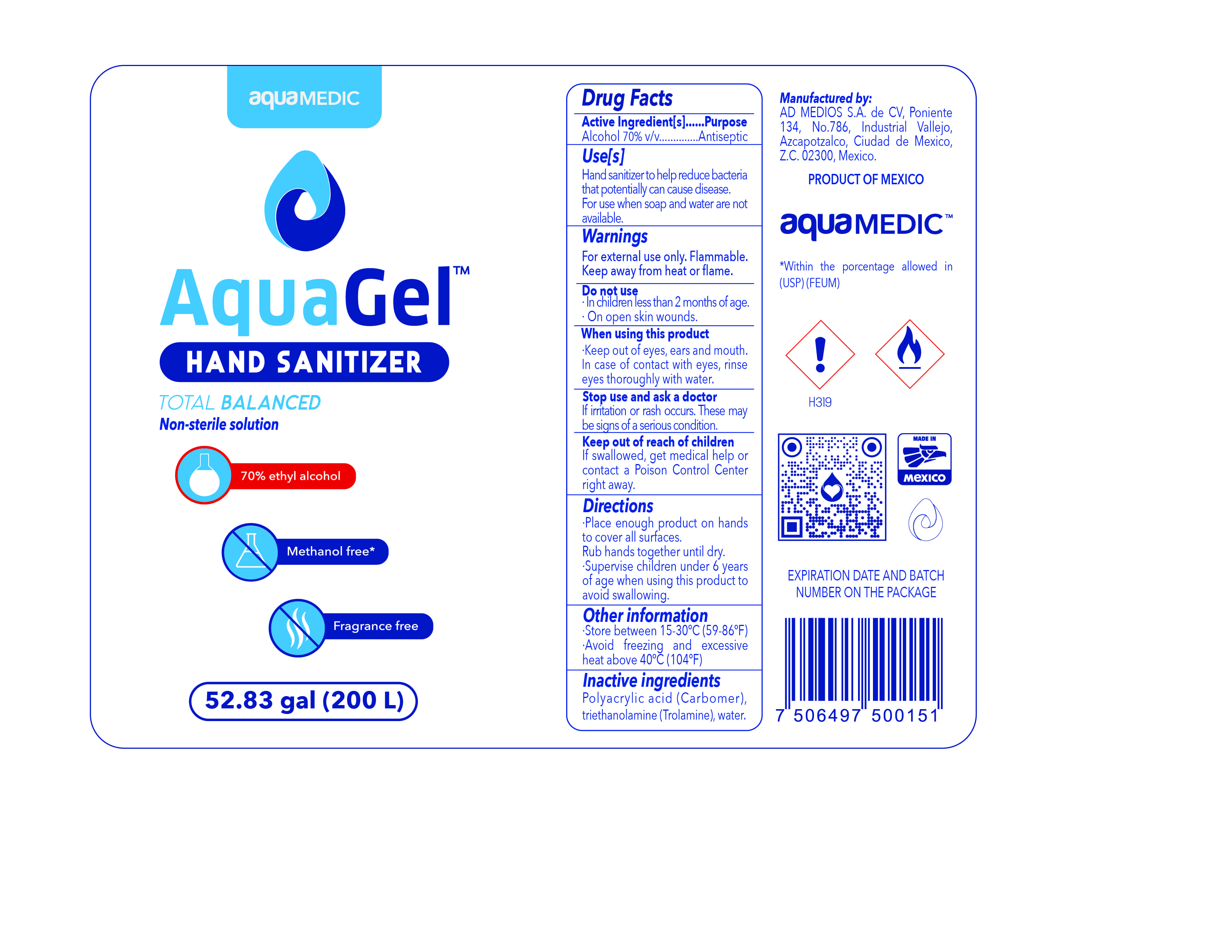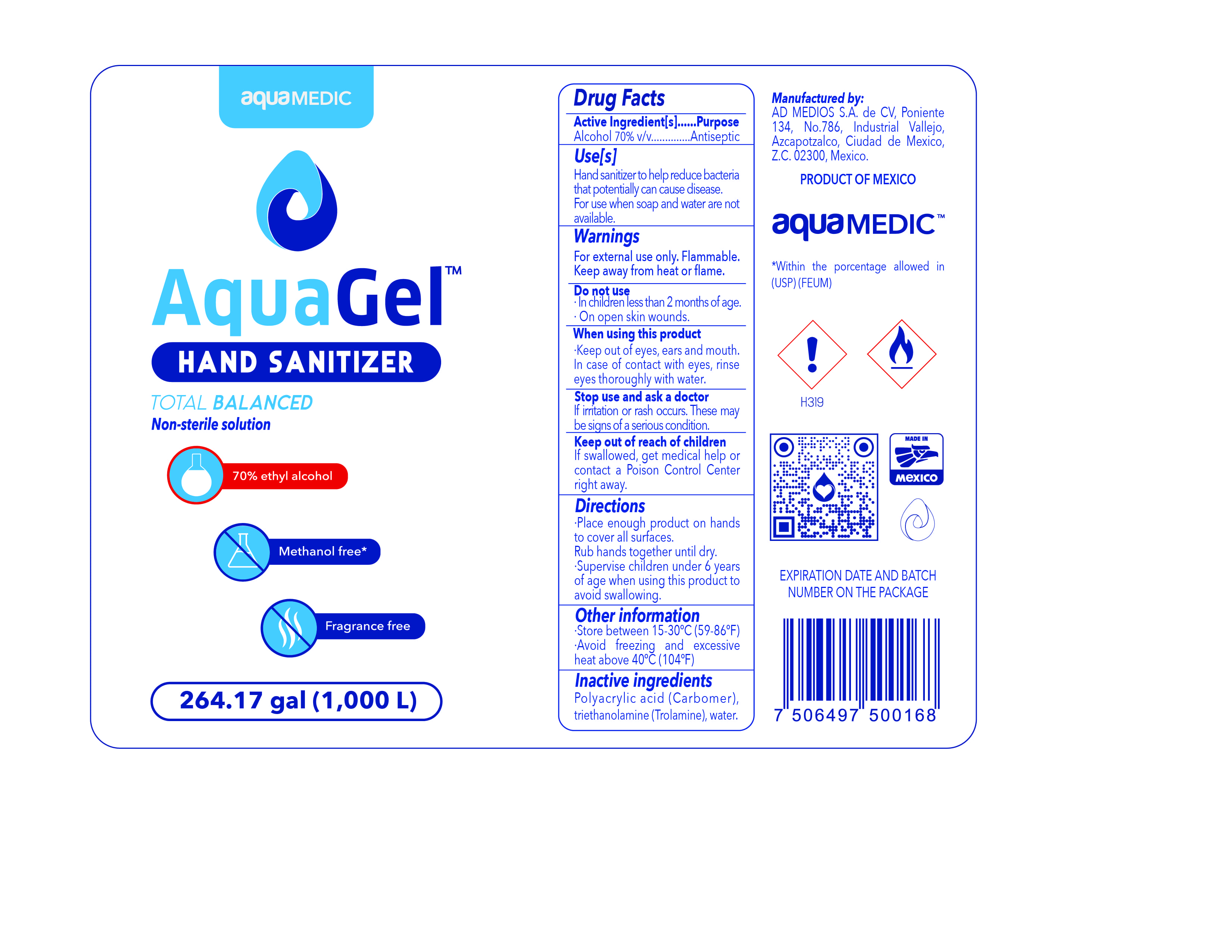 DRUG LABEL: Aqua Gel
NDC: 77739-001 | Form: GEL
Manufacturer: AD MEDIOS, S.A. DE C.V.
Category: otc | Type: HUMAN OTC DRUG LABEL
Date: 20210126

ACTIVE INGREDIENTS: ALCOHOL 70 mL/100 mL
INACTIVE INGREDIENTS: POLYACRYLIC ACID (8000 MW) 0.03 mL/100 mL; TROLAMINE 1 mL/100 mL; WATER 28.97 mL/100 mL

Active Ingredient(s)

Alcohol 70% v/v. Purpose: Antiseptic

Purpose

Antiseptic, Hand Sanitizer

Use

Hand Sanitizer to help reduce bacteria that potentially can cause disease. For use when soap and water are not available.

Warnings

For external use only. Flammable. Keep away from heat or flame

Do not use

- in children less than 2 months of age
- on open skin wounds

When using this product keep out of eyes, ears, and mouth. In case of contact with eyes, rinse eyes thoroughly with water.
Stop use and ask a doctor if irritation or rash occurs. These may be signs of a serious condition.
Keep out of reach of children. If swallowed, get medical help or contact a Poison Control Center right away.

Stop use and ask a doctor if irritation or rash occurs. These may be signs of a serious condition.

Keep out of reach of children. If swallowed, get medical help or contact a Poison Control Center right away.

Directions

- Place enough product on hands to cover all surfaces. Rub hands together until dry.
- Supervise children under 6 years of age when using this product to avoid swallowing.

Other information

- Store between 15-30C (59-86F)
- Avoid freezing and excessive heat above 40C (104F)

Inactive ingredients

polyacrylic acid (Carbomer), triethanolamine (Trolamine), water

20 L NDC: 77739-001-01

3780 mL NDC: 77739-001-02

1L NDC: 77739-001-04

500 mL NDC: 77739-001-05

250 mL NDC: 77739-001-06

5L NDC: 77739-001-12

125 mL NDC: 77739-001-08

60 mL NDC: 77739-001-09

200L NDC: 77739-001-10

1000L 77739-001-11